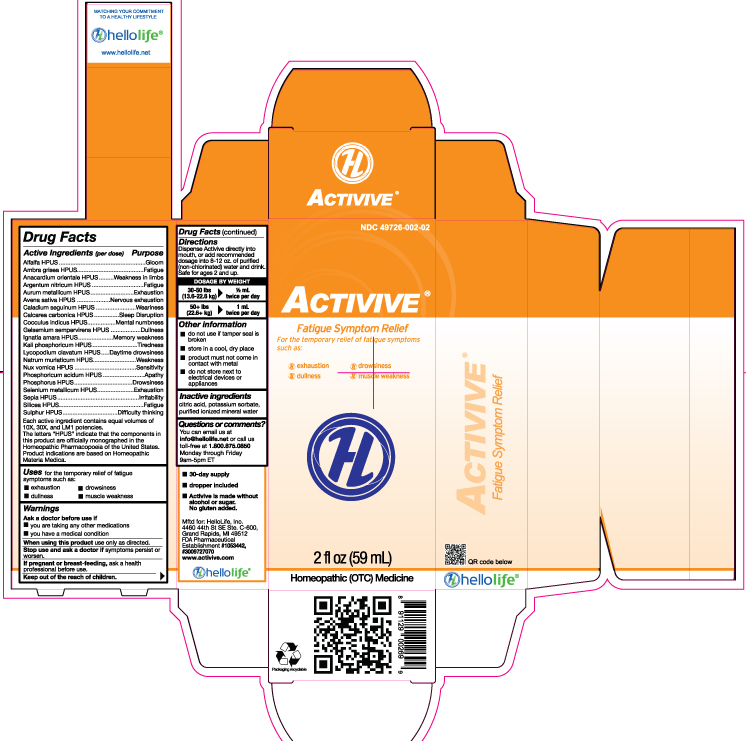 DRUG LABEL: Activive
NDC: 49726-002 | Form: LIQUID
Manufacturer: Hello Life, Inc.
Category: homeopathic | Type: HUMAN OTC DRUG LABEL
Date: 20181227

ACTIVE INGREDIENTS: ALFALFA 10 [hp_X]/59 mL; AMBERGRIS 10 [hp_X]/59 mL; SEMECARPUS ANACARDIUM JUICE 10 [hp_X]/59 mL; SILVER NITRATE 10 [hp_X]/59 mL; GOLD 10 [hp_X]/59 mL; AVENA SATIVA FLOWERING TOP 10 [hp_X]/59 mL; DIEFFENBACHIA SEGUINE 10 [hp_X]/59 mL; OYSTER SHELL CALCIUM CARBONATE, CRUDE 10 [hp_X]/59 mL; ANAMIRTA COCCULUS SEED 10 [hp_X]/59 mL; GELSEMIUM SEMPERVIRENS ROOT 10 [hp_X]/59 mL; STRYCHNOS IGNATII SEED 10 [hp_X]/59 mL; POTASSIUM PHOSPHATE, DIBASIC 10 [hp_X]/59 mL; LYCOPODIUM CLAVATUM SPORE 10 [hp_X]/59 mL; SODIUM CHLORIDE 10 [hp_X]/59 mL; STRYCHNOS NUX-VOMICA SEED 10 [hp_X]/59 mL; PHOSPHORIC ACID 10 [hp_X]/59 mL; PHOSPHORUS 10 [hp_X]/59 mL; SELENIUM 10 [hp_X]/59 mL; SEPIA OFFICINALIS JUICE 10 [hp_X]/59 mL; SILICON DIOXIDE 10 [hp_X]/59 mL; SULFUR 10 [hp_X]/59 mL
INACTIVE INGREDIENTS: WATER; POTASSIUM SORBATE; CITRIC ACID MONOHYDRATE

Drug Facts

Active Ingredients (per dose)

Alfalfa HPUS

Ambra grisea HPUS

Anacardium orientale HPUS

Argentum nitricum HPUS

Aurum metallicum HPUS

Avena sativa HPUS

Caladium seguinum HPUS

Calcarea carbonica HPUS

Cocculus indicus HPUS

Gelsemium sempervirens HPUS

Ignatia amara HPUS

Kali phosphoricum HPUS

Lycopodium clavatum HPUS

Natrum muriaticum HPUS

Nux vomica HPUS

Phosphoricum acidum HPUS

Phosphorus HPUS

Selenium metallicum HPUS

Sepia HPUS

Silicea HPUS

Sulphur HPUS

Each active ingredient contains equal volumes of 10X, 30X, and LM1 potencies. The letters “HPUS” indicate that the components in this product are officially monographed in the Homeopathic Pharmacopoeia of the United States. Product indications are based on Homeopathic Materia Medica.

Purpose

Alfalfa HPUS..................................Gloom
Ambra grisea HPUS........................Fatigue
Anacardium orientale HPUS............Weakness in limbs
Argentum nitricum HPUS................Fatigue
Aurum metallicum HPUS................Exhaustion
Avena sativa HPUS.......................Nervous exhaustion
Caladium seguinum HPUS..............Weariness
Calcarea carbonica HPUS...............Sleep Disruption
Cocculus indicus HPUS..................Mental numbness
Gelsemium sempervirens HPUS......Dullness
Ignatia amara HPUS.......................Memory weakness
Kali phosphoricum HPUS................Tiredness
Lycopodium clavatum HPUS...........Daytime drowsiness
Natrum muriaticum HPUS...............Weakness
Nux vomica HPUS.........................Serenity
Phosphoricum acidum HPUS..........Apathy
Phosphorus HPUS.........................Drowsiness
Selenium metallicum HPUS............Exhaustion
Sepia HPUS..................................Irritability
Silicea HPUS................................Fatigue
Sulphur HPUS...............................Difficulty thinking

Uses

for temporary relief of symptoms of fatigue such as:

- exhaustion
- dullness
- drowsiness
- muscle weakness

Warnings

Ask a doctor before use if

- you are taking any other medications
- you have a medical condition

When using this product use only as directed.

Stop use and ask a doctor if symptoms persist or worsen.

PREGNANCY OR BREAST FEEDING

If pregnant or breast-feeding, ask a health professional before use.

Keep out of the reach of children.

Directions

Dispense Activive directly into mouth, or add recommended dosage into 8-12 oz. of purified (non-chlorinated) water and drink. Safe for ages 2 and up.

DOSAGE BY WEIGHT

30-50 lbs 1/2 mL
(13.6-22.6 kg) twice per day
50+ lbs 1 mL
(22.6+ kg) twice per day

Other information

• do not use if tamper seal is broken
• store in a cool, dry place
• product must not come in contact with metal
• do not store next to electrical devices or appliances

Inactive ingredients

citric acid, potassium sorbate, purified ionized mineral water

Questions or comments?

You can email us at info@hellolife.net or call us toll-free at
1.800.875.0850. Monday through Friday, 9am-5pm ET

DESCRIPTION

- 30 day supply
- dropper included
- Activive is made without alcohol or sugar. No gluten added.

Mftd for: Hello Life, Inc.

4460 44th St. SE Ste. C-600
Grand Rapids, MI 49512
FDA Pharmaceutical Establishment
#1053442, #3009727070

www.activive.com

Principal Display Panel

NDC 49726-002-02

ACTIVIVE™

Fatigue Symptom Relief

For the temporary relief of fatigue symptoms such as:

exhaustiondullnessdrowsinessmuscle weakness

2 fl oz (59 mL)

Homeopathic (OTC) Medicine